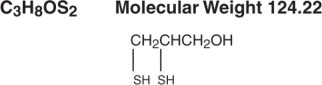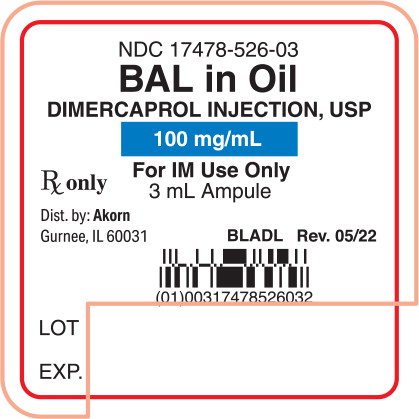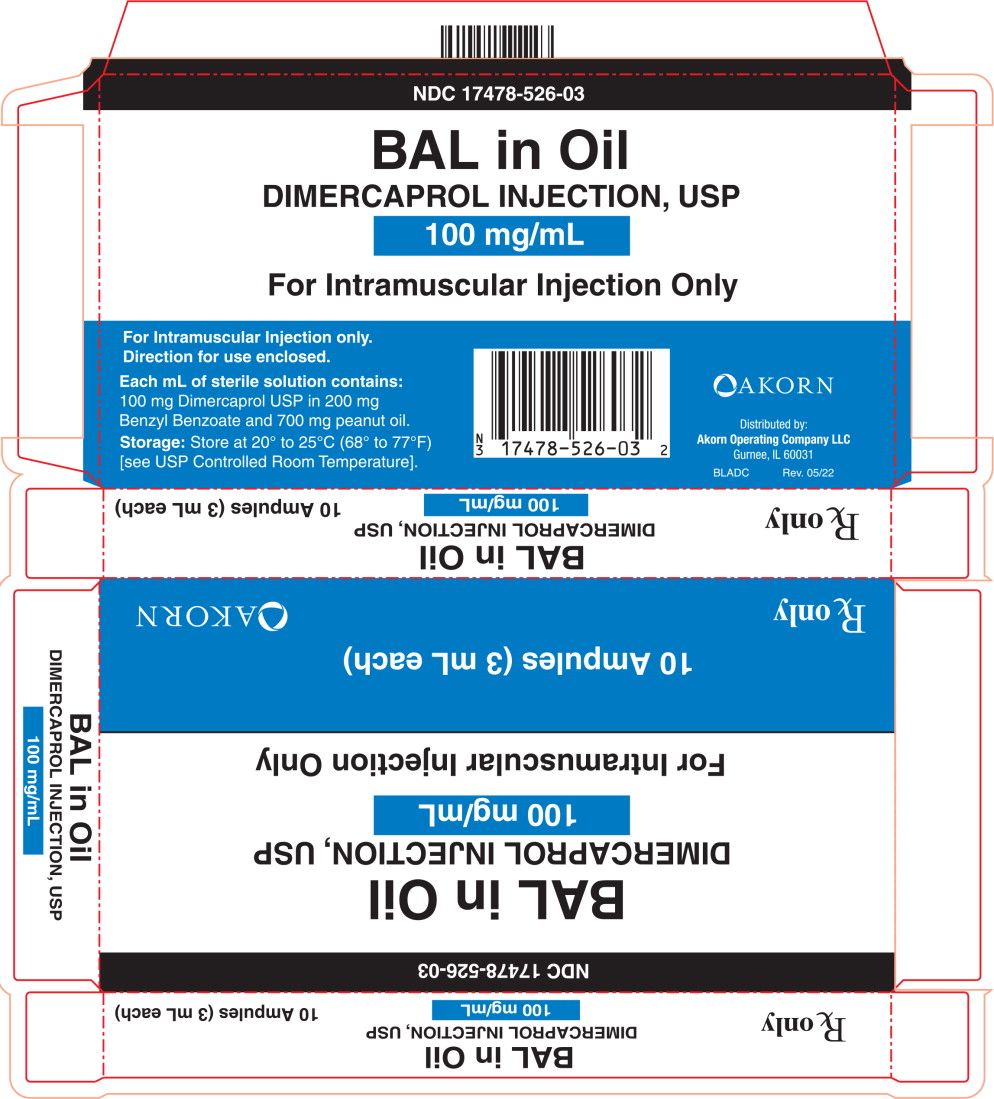 DRUG LABEL: BAL
NDC: 17478-526 | Form: INJECTION
Manufacturer: Akorn
Category: prescription | Type: HUMAN PRESCRIPTION DRUG LABEL
Date: 20220620

ACTIVE INGREDIENTS: Dimercaprol 100 mg/1 mL
INACTIVE INGREDIENTS: Benzyl Benzoate 200 mg/1 mL; Peanut Oil 700 mg/1 mL

BAL in Oil Ampules
DIMERCAPROL INJECTION, USP

BAL (2,3-dimercapto-1-propanol) 10%, Benzyl Benzoate 20%, in Peanut Oil

Rx only

DESCRIPTION

Dimercaprol Injection USP is a colorless or almost colorless liquid chelating agent having a disagreeable, mercaptan-like odor. Each 1 mL sterile BAL in Oil (Dimercaprol Injection USP) contains: 100 mg Dimercaprol in 200 mg Benzyl Benzoate and 700 mg Peanut Oil.

CLINICAL PHARMACOLOGY

The sulfhydryl groups of dimercaprol form complexes with certain heavy metals thus preventing or reversing the metallic binding of sulfhydryl-containing enzymes. The complex is excreted. The sustained presence of dimercaprol promotes continued excretion of the metallic poisons - arsenic, gold and mercury. It is also used in combination with Edetate Calcium Disodium Injection USP to promote the excretion of lead.

INDICATIONS

BAL in Oil (Dimercaprol Injection USP) is indicated in the treatment of arsenic, gold and mercury poisoning. It is indicated in acute lead poisoning when used concomitantly with Edetate Calcium Disodium Injection USP.

Dimercaprol Injection USP is effective for use in acute poisoning by mercury salts if therapy is begun within one or two hours following ingestion. It is not very effective for chronic mercury poisoning.

Dimercaprol Injection USP is of questionable value in poisoning caused by other heavy metals such as antimony and bismuth. It should not be used in iron, cadmium, or selenium poisoning because the resulting dimercaprol-metal complexes are more toxic than the metal alone, especially to the kidneys.

CONTRAINDICATIONS

BAL in Oil (Dimercaprol Injection USP) is contraindicated in most instances of hepatic insufficiency with the exception of postarsenical jaundice. The drug should be discontinued or used only with extreme caution if acute renal insufficiency develops during therapy.

WARNINGS

There may be local pain at the site of the injection. A reaction apparently peculiar to children is fever which may persist during therapy. It occurs in approximately 30% of children. A transient reduction of the percentage of polymorphonuclear leukocytes may also be observed.

PRECAUTIONS

Because the dimercaprol-metal complex breaks down easily in an acid medium, production of an alkaline urine affords protection to the kidney during therapy. Medicinal iron should not be administered to patients under therapy with BAL in Oil (Dimercaprol Injection USP).

BAL in Oil Ampules is formulated with peanut oil. Peanut oil may cause allergic reactions in some individuals. Physicians should use caution in prescribing BAL in Oil Ampules for peanut-sensitive patients. Medication and equipment necessary to treat allergic reactions should be available if the product is administered to peanut-allergic patients.

Pregnancy Category C

Animal reproduction studies have not been conducted with BAL in Oil. It is also not known whether BAL in Oil can cause fetal harm when administered to a pregnant woman, or can affect reproduction capacity. BAL in Oil should be given to a pregnant woman only if clearly needed.

It is not known whether this drug is excreted in human milk. However, because many drugs are excreted in human milk, caution should be exercised when BAL in Oil is administered to a nursing woman.

ADVERSE REACTIONS

One of the most consistent responses to Dimercaprol Injection USP is a rise in blood pressure accompanied by tachycardia. This rise is roughly proportional to the dose administered. Doses larger than those recommended may cause other transitory signs and symptoms in approximate order of frequency as follows: (1) nausea and, in some instance, vomiting; (2) headache; (3) a burning sensation in the lips, mouth and throat; (4) a feeling of constriction, even pain, in the throat, chest, or hands; (5) conjunctivitis, lacrimation, blepharal spasm, rhinorrhea, and salivation; (6) tingling of the hands; (7) a burning sensation in the penis; (8) sweating of the forehead, hands and other areas; (9) abdominal pain; and (10) occasional appearance of painful sterile abscesses. Many of the above symptoms are accompanied by a feeling of anxiety, weakness, and unrest and often are relieved by administration of antihistamine.

DRUG ABUSE AND DEPENDENCE

Dimercaprol Injection USP is not a controlled substance listed in any other Drug Enforcement Administration schedules. Its use is not known to lead to dependence or abuse.

OVERDOSE

Dosage exceeding 5 mg/kg will usually be followed by vomiting, convulsions and stupor, beginning within 30 minutes and subsiding within 6 hours following injection.

AMER. HOSP. FORM. SERV., 64:00, Amer. Soc. Hosp. Pharm., 1977.

DOSAGE AND ADMINISTRATION

By deep intramuscular injection only. For mild arsenic or gold poisoning, 2.5 mg/kg of body weight four times daily for two days, two times on the third day, and once daily thereafter for ten days; for severe arsenic or gold poisoning, 3 mg/kg every four hours for two-days, four times on the third day, then twice daily thereafter for ten days. For mercury poisoning, 5 mg/kg initially, followed by 2.5 mg/kg one or two times daily for ten days. For acute lead encephalopathy, 4 mg/kg body weight is given alone in the first dose and thereafter at four-hour intervals in combination with Edetate Calcium Disodium Injection USP administered at a separate site. For less severe poisoning the dose can be reduced to 3 mg/kg after the first dose. Treatment is maintained for two to seven days depending on clinical response. Successful treatment depends on beginning injections at the earliest possible moment and on the use of adequate amounts at frequent intervals. Other supportive measures should always be used in conjunction with BAL in Oil (Dimercaprol Injection USP) therapy.

BAL in Oil should be inspected visually for particulate matter and discoloration prior to administration.

HOW SUPPLIED

3 mL (100 mg/mL) ampules, box of 10 (NDC 17478-526-03).

STORAGE AND HANDLING

STORAGE: Store at 20° to 25°C (68° to 77°F) [see USP Controlled Room Temperature].

ANIMAL TOXICOLOGY

The intramuscular LD50 in rats is approximately 105 mg/kg; intraperitoneally 140 mg/kg. The intraperitoneal LD80 in mice is approximately 125 mg/kg.

JR. PHARM. EXPER. THER., 87, Supplement Aug. 1946.

Akorn

Distributed by:
Akorn Operating Company LLC
Gurnee, IL 60031

BL00N Rev. 05/22

Principal Display Panel Text for Container Label:

NDC 17478-526-03
BAL in Oil
DIMERCAPROL INJECTION, USP
100 mg/mL
For IM Use Only
Rx only 3 mL Ampule

Principal Display Panel Text for Carton Label:

NDC 17478-526-03
BAL in Oil
DIMERCAPROL INJECTION, USP
100 mg/mL
For Intramuscular Injection Only
10 Ampules (3 mL each)
Rx only Akorn Logo